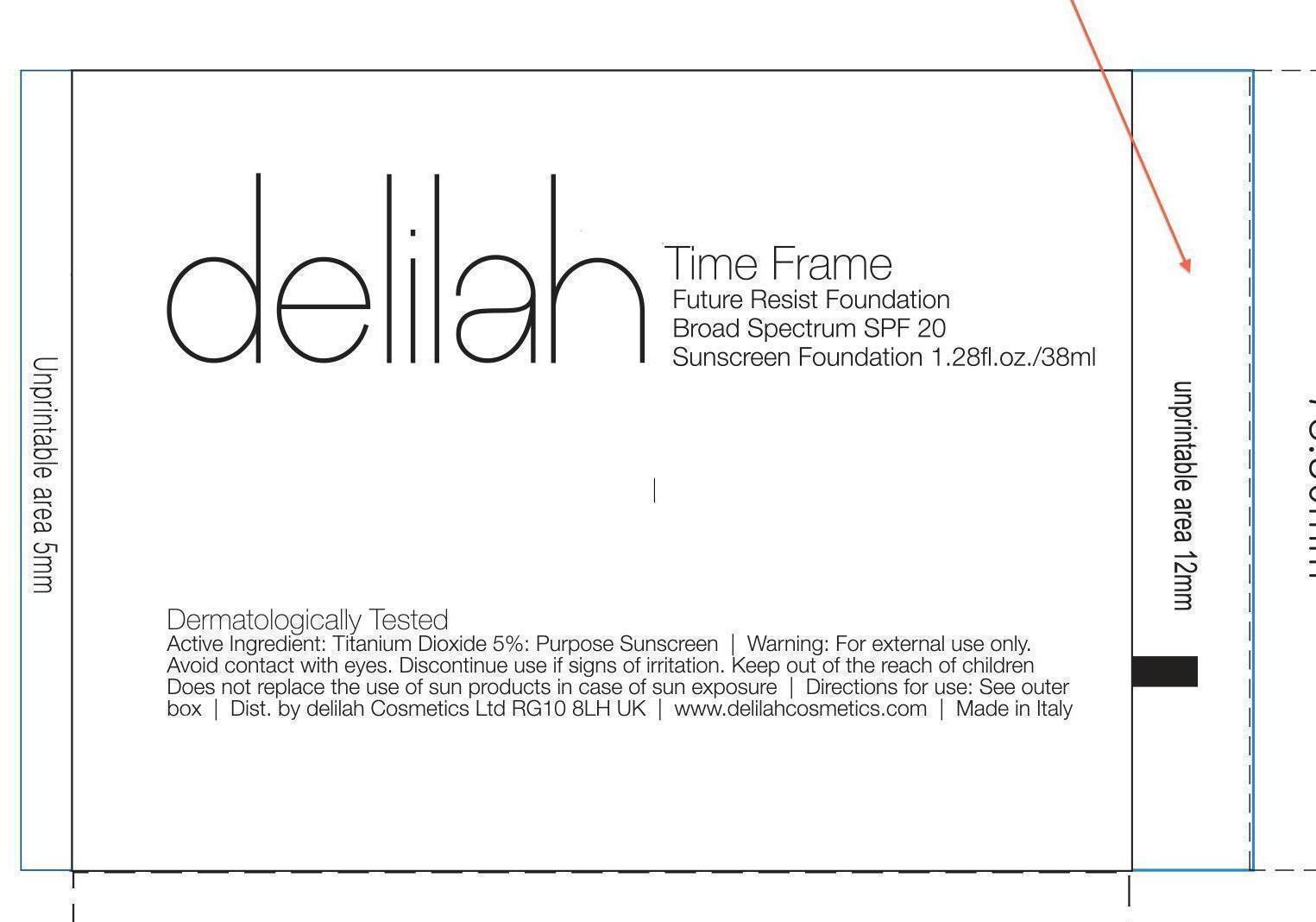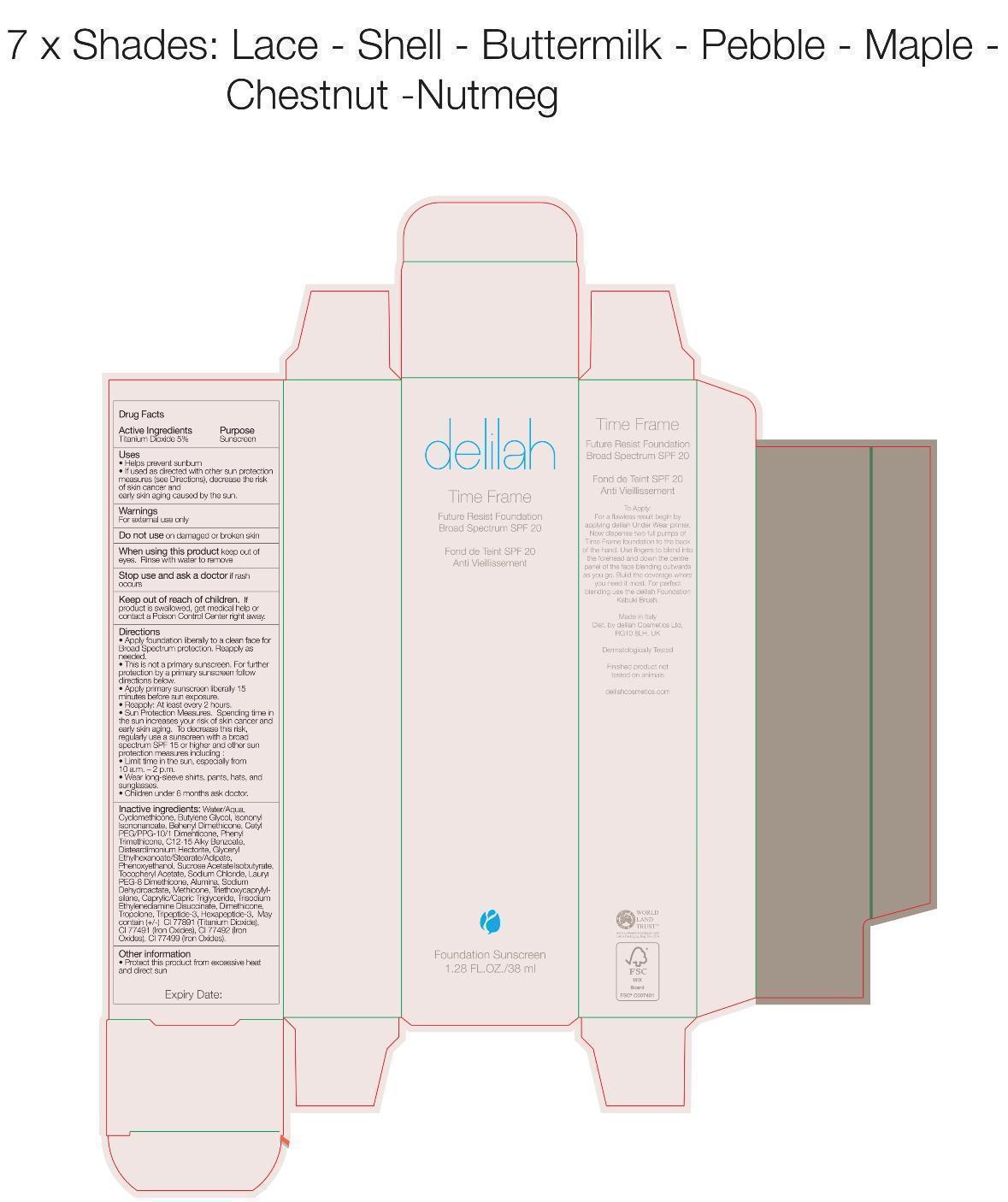 DRUG LABEL: Chestnut Future Resist Foundation Broad Spectrum Foundation
NDC: 69000-024 | Form: LIQUID
Manufacturer: Delilah Cosmetics
Category: otc | Type: HUMAN OTC DRUG LABEL
Date: 20141226

ACTIVE INGREDIENTS: TITANIUM DIOXIDE 5 g/100 mL
INACTIVE INGREDIENTS: WATER; CYCLOMETHICONE; ISONONYL ISONONANOATE; CETYL PEG/PPG-10/1 DIMETHICONE (HLB 2); PHENYL TRIMETHICONE; C12-15 ALKYL BENZOATE; DISTEARDIMONIUM HECTORITE; PHENOXYETHANOL; .ALPHA.-TOCOPHEROL ACETATE; SODIUM CHLORIDE; ALUMINUM OXIDE; SODIUM DEHYDROACETATE; METHICONE (20 CST); TRIETHOXYCAPRYLYLSILANE; MEDIUM-CHAIN TRIGLYCERIDES; DIMETHICONE; TROPOLONE; ACETYL HEXAPEPTIDE-8; FERRIC OXIDE RED; FERRIC OXIDE YELLOW; FERROSOFERRIC OXIDE

Chestnut Delilah Time Frame Future Resist foundation SPF 20

Active Ingredients Purpose

Titanium Dioxide 5% Sunscreen

Uses

Helps prevent Sunburn

If used as directed with other sun protection measures (see Directions), decrease the risk of of skin cancer and early skin aging caused by the sun.

Keep out of reach of children. If product is swallowed, get medical help or contact a Poison Control Center right away.

Stop use and ask a doctor if rash occurs.

Warnings

For external use only

Do not use on damaged or broken skin

When using this product keep out of eyes. Rinse with water to remove

Directions

Apply foundation to a clean face for Broad Spectrum protection. Reapply as needed.

This is not a primary sunscreen. For further protection by a primary sunscreen follow directions below.

Apply primary sunscreen liberally 15 minutes before sun exposure

Reapply: At least 2 hours

Sun Protection Measures. Spending time in the sun increases your risk of skin cancer and early skin aging To decrease this risk, regularly use a sunscreen with a Broad Spectrum SPF 15 or higher and other sun protection measures including:

Limit time in the sun, especially from 10 a.m. - 2p.m.

Wear long-sleeve shirts, pants, hats, and sunglasses

Children under 6 months ask doctor.

INACTIVE INGREDIENT

Inactive Ingredients: Water/Aqua, Cyclomethicone, Butylene Glycol, Isononyl Isononoate, Behenyl Dimethicone, Cetyl PEG/PPG-10/1 Dimethicone, Phenyl Trimethicone, C12-15 Alkyl Benzoate, Disteardimonium Hectorite, Glcyeryl Ethylhexanoate/Stearate/Adipate, Phenoxyethanol, Sucrose Acetyl Isobutyrate, Tocopheryl Acetate, Sodium Chloride, Lauryl PEG-8 Dimethicone, Alumina, Sodium Dehydroacetate, Methicone, Triethoxycaprylylsilane, Caprylic/Capric Triglyceride, Trisodium Ethylenediamine Dissucinate, Dimethicone, Tropolone, Tripeptide-3, Hexapeptide-3, (May contain (+/-) CI 77891 (Titanium Dioxide), CI 77491 (iron oxides), CI 77492 (Iron Oxides), CI 77499 (Iron Oxides).

PACKAGE LABEL

Delilah

Time Frame Future resist Foundation Broad Spectrum SPF 20 Chestnut

Fond de Teint SPF 20 Anti Vieillissement

Foundation Sunscreen

1.28 Fl OZ./36 ml